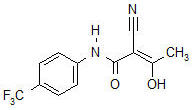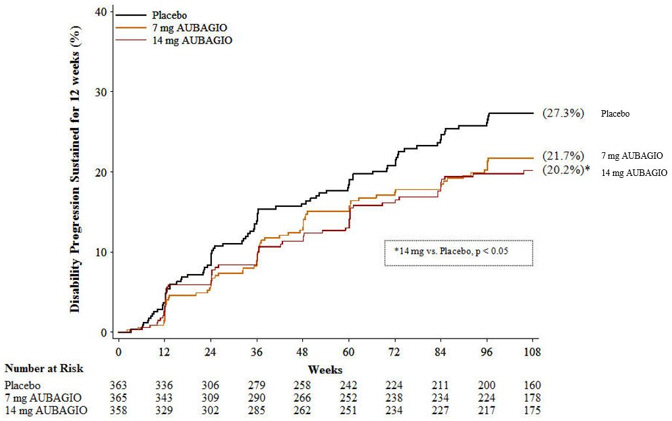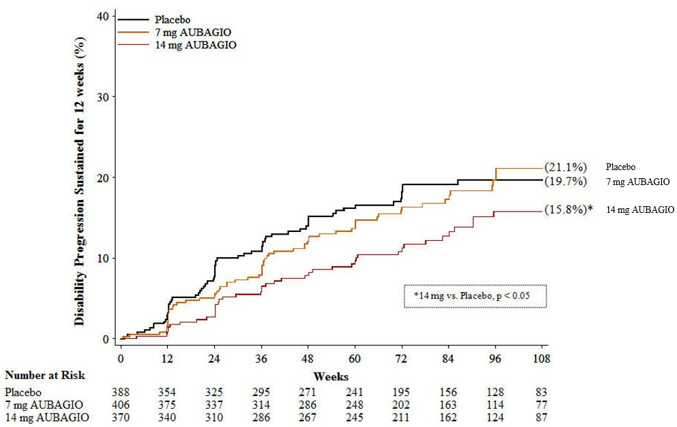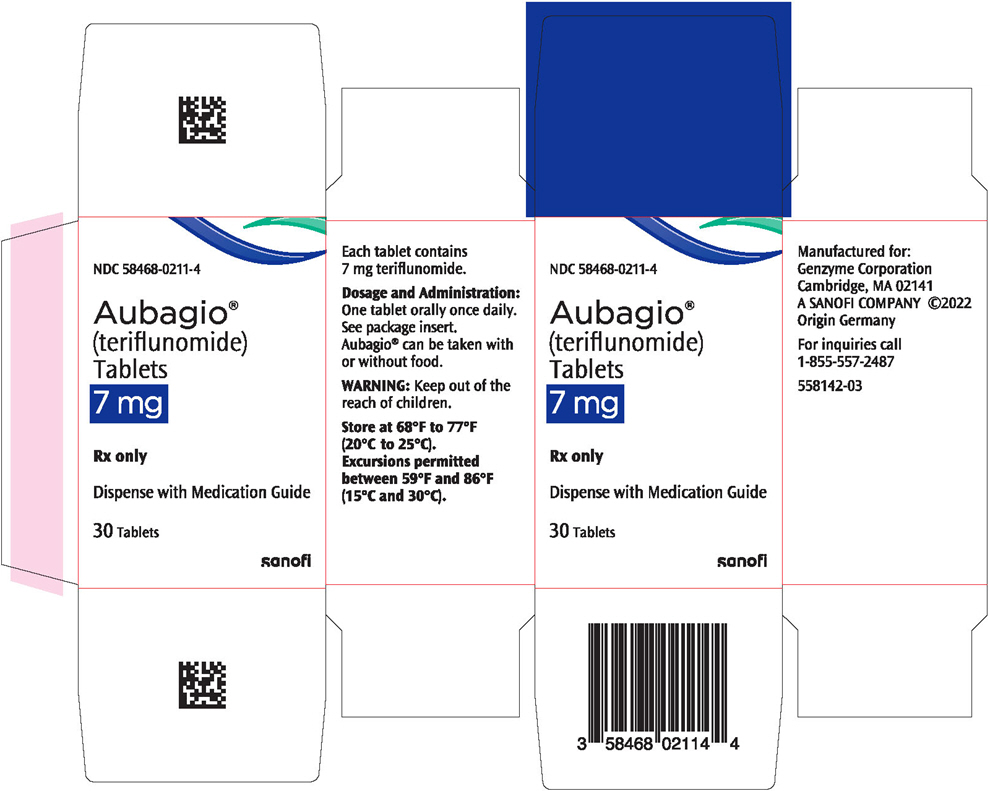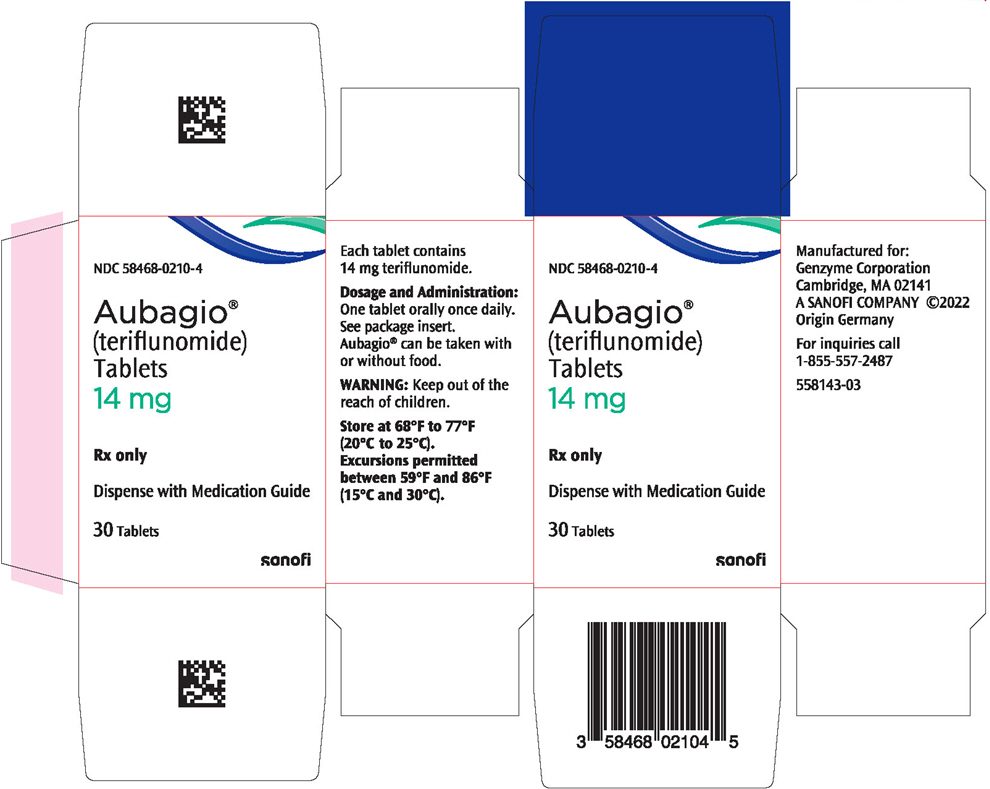 DRUG LABEL: Aubagio
NDC: 58468-0211 | Form: TABLET, FILM COATED
Manufacturer: Genzyme Corporation
Category: prescription | Type: HUMAN PRESCRIPTION DRUG LABEL
Date: 20260220

ACTIVE INGREDIENTS: TERIFLUNOMIDE 7 mg/1 1
INACTIVE INGREDIENTS: LACTOSE MONOHYDRATE; STARCH, CORN; HYDROXYPROPYL CELLULOSE, UNSPECIFIED; MICROCRYSTALLINE CELLULOSE; SODIUM STARCH GLYCOLATE TYPE A CORN; MAGNESIUM STEARATE; HYPROMELLOSE, UNSPECIFIED; TITANIUM DIOXIDE; TALC; POLYETHYLENE GLYCOL, UNSPECIFIED; FD&C BLUE NO. 2; FERRIC OXIDE YELLOW

HIGHLIGHTS OF PRESCRIBING INFORMATION

These highlights do not include all the information needed to use AUBAGIO® safely and effectively. See full prescribing information for AUBAGIO.
AUBAGIO (teriflunomide) tablets, for oral use
Initial U.S. Approval: 2012

WARNING: HEPATOTOXICITY and EMBRYOFETAL TOXICITY

See full prescribing information for complete boxed warning.

- Hepatotoxicity

Clinically significant and potentially life-threatening liver injury, including acute liver failure requiring transplant, has been reported in patients treated with AUBAGIO in the postmarketing setting (5.1). Concomitant use of AUBAGIO with other hepatotoxic drugs may increase the risk of severe liver injury. Obtain transaminase and bilirubin levels within 6 months before initiation of AUBAGIO and monitor ALT levels at least monthly for six months (5.1). If drug induced liver injury is suspected, discontinue AUBAGIO and start accelerated elimination procedure (5.3).

- Embryofetal Toxicity

Teratogenicity and embryolethality occurred in animals administered teriflunomide (5.2, 8.1). Exclude pregnancy prior to initiating AUBAGIO therapy (4, 5.2, 8.1, 8.3). Advise use of effective contraception in females of reproductive potential during treatment and during an accelerated drug elimination procedure (4, 5.2, 5.3, 8.1, 8.3). Stop AUBAGIO and use an accelerated drug elimination procedure if the patient becomes pregnant (5.2, 5.3, 8.1).

RECENT MAJOR CHANGES

Warnings and Precautions (5.8) | 2/2026

1 INDICATIONS AND USAGE

AUBAGIO is a pyrimidine synthesis inhibitor indicated for the treatment of relapsing forms of multiple sclerosis (MS), to include clinically isolated syndrome, relapsing-remitting disease, and active secondary progressive disease, in adults. (1)

2 DOSAGE AND ADMINISTRATION

7 mg or 14 mg orally once daily, with or without food. (2)

3 DOSAGE FORMS AND STRENGTHS

7 mg and 14 mg film-coated tablets (3)

4 CONTRAINDICATIONS

- Severe hepatic impairment (4, 5.1)
- Pregnancy (4, 5.2, 8.1)
- Hypersensitivity (4, 5.5)
- Current leflunomide treatment (4)

5 WARNINGS AND PRECAUTIONS

- Elimination of AUBAGIO can be accelerated by administration of cholestyramine or activated charcoal for 11 days. (5.3)
- AUBAGIO may decrease WBC. A recent CBC should be available before starting AUBAGIO. Monitor for signs and symptoms of infection. Consider suspending treatment with AUBAGIO in case of serious infection. Do not start AUBAGIO in patients with active infections. (5.4)
- Stop AUBAGIO if patient has anaphylaxis, angioedema, Stevens-Johnson syndrome, toxic epidermal necrolysis, drug reaction with eosinophilia and systemic symptoms; initiate rapid elimination. (5.3, 5.5, 5.6, 5.7)
- Cutaneous or mucocutaneous ulcers/impaired wound healing: If ulcer or impaired wound healing is suspected, consider discontinuation of AUBAGIO treatment and an accelerated drug elimination procedure. (5.8)
- If patient develops symptoms consistent with peripheral neuropathy, evaluate patient and consider discontinuing AUBAGIO. (5.9)
- AUBAGIO may increase blood pressure. Measure blood pressure at treatment initiation and monitor blood pressure during treatment. (5.10)

6 ADVERSE REACTIONS

Most common adverse reactions (≥10% and ≥2% greater than placebo): headache, diarrhea, nausea, alopecia, increase in ALT. (6)
To report SUSPECTED ADVERSE REACTIONS, contact Genzyme Corporation at 1-800-745-4447 or FDA at 1-800-FDA-1088 or www.fda.gov/medwatch.

7 DRUG INTERACTIONS

- Drugs metabolized by CYP2C8 and OAT3 transporters: Monitor patients because teriflunomide may increase exposure of these drugs. (7)
- Teriflunomide may increase exposure of ethinylestradiol and levonorgestrel. Choose an appropriate oral contraceptive. (7)
- Drugs metabolized by CYP1A2: Monitor patients because teriflunomide may decrease exposure of these drugs. (7)
- Warfarin: Monitor INR as teriflunomide may decrease INR. (7)
- Drugs metabolized by BCRP and OATP1B1/B3 transporters: Monitor patients because teriflunomide may increase exposure of these drugs. (7)
- Rosuvastatin: The dose of rosuvastatin should not exceed 10 mg once daily in patients taking AUBAGIO. (7)

FULL PRESCRIBING INFORMATION

WARNING: HEPATOTOXICITY and EMBRYOFETAL TOXICITY

- Hepatotoxicity

Clinically significant and potentially life-threatening liver injury, including acute liver failure requiring transplant, has been reported in patients treated with AUBAGIO in the postmarketing setting [see Warnings and Precautions (5.1)]. Concomitant use of AUBAGIO with other hepatotoxic drugs may increase the risk of severe liver injury.

Obtain transaminase and bilirubin levels within 6 months before initiation of AUBAGIO therapy. Monitor ALT levels at least monthly for six months after starting AUBAGIO [see Warnings and Precautions (5.1)]. If drug induced liver injury is suspected, discontinue AUBAGIO and start an accelerated elimination procedure with cholestyramine or charcoal [see Warnings and Precautions (5.3)]. AUBAGIO is contraindicated in patients with severe hepatic impairment [see Contraindications (4)]. Patients with pre-existing liver disease may be at increased risk of developing elevated serum transaminases when taking AUBAGIO.

- Embryofetal Toxicity

AUBAGIO is contraindicated for use in pregnant women and in females of reproductive potential who are not using effective contraception because of the potential for fetal harm. Teratogenicity and embryolethality occurred in animals at plasma teriflunomide exposures lower than that in humans. Exclude pregnancy before the start of treatment with AUBAGIO in females of reproductive potential. Advise females of reproductive potential to use effective contraception during AUBAGIO treatment and during an accelerated drug elimination procedure after AUBAGIO treatment. Stop AUBAGIO and use an accelerated drug elimination procedure if the patient becomes pregnant [see Contraindications (4), Warnings and Precautions (5.2, 5.3), Use in Specific Populations (8.1, 8.3), and Clinical Pharmacology (12.3)].

1 INDICATIONS AND USAGE

AUBAGIO® is indicated for the treatment of relapsing forms of multiple sclerosis (MS), to include clinically isolated syndrome, relapsing-remitting disease, and active secondary progressive disease, in adults.

2 DOSAGE AND ADMINISTRATION

The recommended dose of AUBAGIO is 7 mg or 14 mg orally once daily. AUBAGIO can be taken with or without food.

Monitoring to Assess Safety

- Obtain transaminase and bilirubin levels within 6 months before initiation of AUBAGIO therapy. Monitor ALT levels at least monthly for six months after starting AUBAGIO [see Warnings and Precautions (5.1)].
- Obtain a complete blood cell count (CBC) within 6 months before the initiation of treatment with AUBAGIO. Further monitoring should be based on signs and symptoms of infection [see Warnings and Precautions (5.4)].
- Prior to initiating AUBAGIO, screen patients for latent tuberculosis infection with a tuberculin skin test or blood test for mycobacterium tuberculosis infection [see Warnings and Precautions (5.4)].
- Exclude pregnancy prior to initiation of treatment with AUBAGIO in females of reproductive potential [see Warnings and Precautions (5.2)].
- Check blood pressure before start of AUBAGIO treatment and periodically thereafter [see Warnings and Precautions (5.10)].

3 DOSAGE FORMS AND STRENGTHS

AUBAGIO is available as 7 mg and 14 mg tablets.

The 14 mg tablet is a pale blue to pastel blue, pentagonal film-coated tablet with the dose strength "14" imprinted on one side and engraved with the corporate logo on the other side. Each tablet contains 14 mg of teriflunomide.

The 7 mg tablet is a very light greenish-bluish grey to pale greenish-blue, hexagonal film-coated tablet with the dose strength "7" imprinted on one side and engraved with the corporate logo on the other side. Each tablet contains 7 mg of teriflunomide.

4 CONTRAINDICATIONS

AUBAGIO is contraindicated in/with:

- Patients with severe hepatic impairment [see Warnings and Precautions (5.1)].
- Pregnant women and females of reproductive potential not using effective contraception. AUBAGIO may cause fetal harm [see Warnings and Precautions (5.2, 5.3) and Use in Specific Populations (8.1)].
- Patients with a history of a hypersensitivity reaction to teriflunomide, leflunomide, or to any of the inactive ingredients in AUBAGIO. Reactions have included anaphylaxis, angioedema, and serious skin reactions [see Warnings and Precautions (5.5)].
- Coadministration with leflunomide [see Clinical Pharmacology (12.3)].

5 WARNINGS AND PRECAUTIONS

5.1 Hepatotoxicity

Clinically significant and potentially life-threatening liver injury, including acute liver failure requiring transplant, has been reported in patients treated with AUBAGIO in the postmarketing setting. Patients with pre-existing liver disease and patients taking other hepatotoxic drugs may be at increased risk for developing liver injury when taking AUBAGIO. Clinically significant liver injury can occur at any time during treatment with AUBAGIO.

Patients with pre-existing acute or chronic liver disease, or those with serum alanine aminotransferase (ALT) greater than two times the upper limit of normal (ULN) before initiating treatment, should not normally be treated with AUBAGIO. AUBAGIO is contraindicated in patients with severe hepatic impairment [see Contraindications (4)].

In placebo-controlled trials in adult patients, ALT greater than three times the ULN occurred in 61/1045 (5.8%) and 62/1002 (6.2%) of patients receiving AUBAGIO 7 mg and 14 mg, respectively, and 38/997 (3.8%) of patients receiving placebo, during the treatment period. These elevations occurred mostly within the first year of treatment. Half of the cases returned to normal without drug discontinuation. In clinical trials, if ALT elevation was greater than three times the ULN on two consecutive tests, AUBAGIO was discontinued and patients underwent an accelerated elimination procedure [see Warnings and Precautions (5.3)]. Of the patients who underwent discontinuation and accelerated elimination in controlled trials, half returned to normal or near normal values within 2 months.

One patient in the controlled trials in adult patients developed ALT 32 times the ULN and jaundice 5 months after initiation of AUBAGIO 14 mg treatment. The patient was hospitalized for 5 weeks and recovered after plasmapheresis and cholestyramine accelerated elimination procedure. AUBAGIO-induced liver injury in this patient could not be ruled out.

Obtain serum transaminase and bilirubin levels within 6 months before initiation of AUBAGIO therapy. Monitor ALT levels at least monthly for six months after starting AUBAGIO. Consider additional monitoring when AUBAGIO is given with other potentially hepatotoxic drugs.

Consider discontinuing AUBAGIO if serum transaminase increase (greater than three times the ULN) is confirmed. Monitor serum transaminase and bilirubin on AUBAGIO therapy, particularly in patients who develop symptoms suggestive of hepatic dysfunction, such as unexplained nausea, vomiting, abdominal pain, fatigue, anorexia, or jaundice and/or dark urine. If liver injury is suspected to be AUBAGIO-induced, discontinue AUBAGIO and start an accelerated elimination procedure [see Warnings and Precautions (5.3)] and monitor liver tests weekly until normalized. If AUBAGIO-induced liver injury is unlikely because some other probable cause has been found, resumption of AUBAGIO therapy may be considered.

5.2 Embryofetal Toxicity

AUBAGIO may cause fetal harm when administered to a pregnant woman. Teratogenicity and embryofetal lethality occurred in animal reproduction studies in multiple animal species at plasma teriflunomide exposures similar to or lower than that in humans at the maximum recommended human dose (MRHD) of 14 mg/day [see Use in Specific Populations (8.1)].

AUBAGIO is contraindicated for use in pregnant women and in females of reproductive potential not using effective contraception [see Contraindications (4)]. Exclude pregnancy before starting treatment with AUBAGIO in females of reproductive potential [see Dosage and Administration (2)]. Advise females of reproductive potential to use effective contraception during AUBAGIO treatment and during an accelerated drug elimination procedure after AUBAGIO treatment [see Use in Specific Populations (8.3)]. If a woman becomes pregnant while taking AUBAGIO, stop treatment with AUBAGIO, apprise the patient of the potential risk to a fetus, and perform an accelerated drug elimination procedure to achieve a plasma teriflunomide concentration of less than 0.02 mg/L [see Warnings and Precautions (5.3)].

Upon discontinuing AUBAGIO, it is recommended that all females of reproductive potential undergo an accelerated drug elimination procedure. Women receiving AUBAGIO treatment who wish to become pregnant must discontinue AUBAGIO and undergo an accelerated drug elimination procedure, which includes verification that plasma concentrations of teriflunomide are less than 0.02 mg/L (0.02 mcg/mL). Men wishing to father a child should also discontinue use of AUBAGIO and either undergo an accelerated elimination procedure or wait until verification that the plasma teriflunomide concentration is less than 0.02 mg/L (0.02 mcg/mL) [see Use in Specific Populations (8.3)]. Based on animal data, human plasma concentrations of teriflunomide of less than 0.02 mg/L (0.02 mcg/mL) are expected to have minimal embryofetal risk [see Contraindications (4), Warnings and Precautions (5.3), and Use in Specific Populations (8.1)].

5.3 Procedure for Accelerated Elimination of Teriflunomide

Teriflunomide is eliminated slowly from the plasma [see Clinical Pharmacology (12.3)]. Without an accelerated elimination procedure, it takes on average 8 months to reach plasma concentrations less than 0.02 mg/L, although because of individual variations in drug clearance it may take as long as 2 years. An accelerated elimination procedure could be used at any time after discontinuation of AUBAGIO. Elimination can be accelerated by either of the following procedures:

- Administration of cholestyramine 8 g every 8 hours for 11 days. If cholestyramine 8 g three times a day is not well tolerated, cholestyramine 4 g three times a day can be used.
- Administration of 50 g oral activated charcoal powder every 12 hours for 11 days.

If either elimination procedure is poorly tolerated, treatment days do not need to be consecutive unless there is a need to lower teriflunomide plasma concentration rapidly.

At the end of 11 days, both regimens successfully accelerated teriflunomide elimination, leading to more than 98% decrease in teriflunomide plasma concentrations.

Use of the accelerated elimination procedure may potentially result in return of disease activity if the patient had been responding to AUBAGIO treatment.

5.4 Bone Marrow Effects/Immunosuppression Potential/Infections

Bone Marrow Effects

A mean decrease compared to baseline in white blood cell (WBC) count of approximately 15% (mainly neutrophils and lymphocytes) and in platelet count of approximately 10% was observed in placebo-controlled trials in adult patients with 7 mg and 14 mg of AUBAGIO. The decrease in mean WBC count occurred during the first 6 weeks and WBC count remained low during treatment. In placebo-controlled studies in adult patients, neutrophil count <1.5 × 10^9/L was observed in 12% and 16% of patients receiving AUBAGIO 7 mg and 14 mg, respectively, compared with 7% of patients receiving placebo; lymphocyte count <0.8 × 10^9/L was observed in 10% and 12% of patients receiving AUBAGIO 7 mg and 14 mg, respectively, compared with 6% of patients receiving placebo. No cases of serious pancytopenia were reported in premarketing clinical trials of AUBAGIO but rare cases of pancytopenia and agranulocytosis have been reported in the postmarketing setting with leflunomide. A similar risk would be expected for AUBAGIO [see Clinical Pharmacology (12.3)]. Cases of thrombocytopenia with AUBAGIO, including rare cases with platelet counts less than 50,000/mm^3, have been reported in the postmarketing setting. Obtain a complete blood cell count (CBC) within 6 months before the initiation of treatment with AUBAGIO. Further monitoring should be based on signs and symptoms suggestive of bone marrow suppression.

Risk of Infection/Tuberculosis Screening

Patients with active acute or chronic infections should not start treatment until the infection(s) is resolved. If a patient develops a serious infection consider suspending treatment with AUBAGIO and using an accelerated elimination procedure. Reassess the benefits and risks prior to resumption of therapy. Instruct patients receiving AUBAGIO to report symptoms of infections to a physician.

AUBAGIO is not recommended for patients with severe immunodeficiency, bone marrow disease, or severe, uncontrolled infections. Medications like AUBAGIO that have immunosuppression potential may cause patients to be more susceptible to infections, including opportunistic infections.

In placebo-controlled studies of AUBAGIO in adult patients, no overall increase in the risk of serious infections was observed with AUBAGIO 7 mg (2.2%) or 14 mg (2.7%) compared to placebo (2.2%).

However, one fatal case of klebsiella pneumonia sepsis occurred in a patient taking AUBAGIO 14 mg for 1.7 years. Fatal infections have been reported in the postmarketing setting in patients receiving leflunomide, especially Pneumocystis jirovecii pneumonia and aspergillosis. Most of the reports were confounded by concomitant immunosuppressant therapy and/or comorbid illness which, in addition to rheumatoid disease, may predispose patients to infection. In clinical studies with AUBAGIO, cytomegalovirus hepatitis reactivation has been observed.

In clinical studies with AUBAGIO in adult patients, cases of tuberculosis have been observed. Prior to initiating AUBAGIO, screen patients for latent tuberculosis infection with a tuberculin skin test or with a blood test for mycobacterium tuberculosis infection. AUBAGIO has not been studied in patients with a positive tuberculosis screen, and the safety of AUBAGIO in individuals with latent tuberculosis infection is unknown. For patients testing positive in tuberculosis screening, treat by standard medical practice prior to therapy with AUBAGIO.

Vaccination

No clinical data are available on the efficacy and safety of live vaccinations in patients taking AUBAGIO. Vaccination with live vaccines is not recommended. The long half-life of AUBAGIO should be considered when contemplating administration of a live vaccine after stopping AUBAGIO.

Malignancy

The risk of malignancy, particularly lymphoproliferative disorders, is increased with the use of some immunosuppressive medications. There is a potential for immunosuppression with AUBAGIO. No apparent increase in the incidence of malignancies and lymphoproliferative disorders was reported in the AUBAGIO clinical trials, but larger and longer-term studies would be needed to determine whether there is an increased risk of malignancy or lymphoproliferative disorders with AUBAGIO.

5.5 Hypersensitivity Reactions

AUBAGIO can cause anaphylaxis and severe allergic reactions [see Contraindications (4)]. Signs and symptoms have included dyspnea, urticaria, and angioedema including lips, eyes, throat, and tongue.

Inform patients of the signs and symptoms of anaphylaxis and angioedema.

5.6 Serious Skin Reactions

Cases of serious skin reactions, sometimes fatal, including Stevens-Johnson syndrome (SJS), toxic epidermal necrolysis (TEN), and drug reaction with eosinophilia and systemic symptoms (DRESS) [see Warnings and Precautions (5.7)], have been reported with AUBAGIO. Fatal outcomes were reported in one case of TEN and one case of DRESS.

Inform patients of the signs and symptoms that may signal a serious skin reaction. Instruct patients to discontinue AUBAGIO and seek immediate medical care should these signs and symptoms occur. Unless the reaction is clearly not drug related, discontinue AUBAGIO and begin an accelerated elimination procedure immediately [see Warnings and Precautions (5.3)]. In such cases, patients should not be re-exposed to teriflunomide [see Contraindications (4)].

5.7 Drug Reaction with Eosinophilia and Systemic Symptoms

Drug reaction with eosinophilia and systemic symptoms (DRESS), also known as multiorgan hypersensitivity, has occurred with AUBAGIO. One fatal case of DRESS that occurred in close temporal association (34 days) with the initiation of AUBAGIO treatment has been reported in the postmarketing setting. DRESS typically, although not exclusively, presents with fever, rash, lymphadenopathy and/or facial swelling, in association with other organ system involvement, such as hepatitis, nephritis, hematologic abnormalities, myocarditis, or myositis, sometimes resembling an acute viral infection. Eosinophilia is often present. This disorder is variable in its expression, and other organ systems not noted here may be involved. It is important to note that early manifestations of hypersensitivity (e.g., fever, lymphadenopathy) may be present even though rash is not evident. If such signs or symptoms are present, the patient should be evaluated immediately.

Discontinue AUBAGIO, unless an alternative etiology for the signs or symptoms is established, and begin an accelerated elimination procedure immediately [see Warnings and Precautions (5.3)]. In such cases, patients should not be re-exposed to teriflunomide [see Contraindications (4)].

5.8 Cutaneous or Mucocutaneous Ulcers and Impaired Wound Healing

Cutaneous or mucocutaneous ulcers and impaired wound healing have been reported in patients during therapy with AUBAGIO. If an AUBAGIO-associated ulcer is suspected, if ulcers persist despite appropriate therapy, or if there is a high risk for impaired wound healing after surgery, consider AUBAGIO discontinuation and an accelerated drug elimination procedure [see Warnings and Precautions (5.3)]. The decision to resume AUBAGIO should be based on clinical judgment of adequate wound healing.

5.9 Peripheral Neuropathy

In placebo-controlled studies in adult patients, peripheral neuropathy, including both polyneuropathy and mononeuropathy (e.g., carpal tunnel syndrome), occurred more frequently in patients taking AUBAGIO than in patients taking placebo. The incidence of peripheral neuropathy confirmed by nerve conduction studies was 1.4% (13 patients) and 1.9% (17 patients) of patients receiving 7 mg and 14 mg of AUBAGIO, respectively, compared with 0.4% receiving placebo (4 patients). Treatment was discontinued in 0.7% (8 patients) with confirmed peripheral neuropathy (3 patients receiving AUBAGIO 7 mg and 5 patients receiving AUBAGIO 14 mg). Five of them recovered following treatment discontinuation. Not all cases of peripheral neuropathy resolved with continued treatment. Peripheral neuropathy also occurred in patients receiving leflunomide.

Age older than 60 years, concomitant neurotoxic medications, and diabetes may increase the risk for peripheral neuropathy. If a patient taking AUBAGIO develops symptoms consistent with peripheral neuropathy, such as bilateral numbness or tingling of hands or feet, consider discontinuing AUBAGIO therapy and performing an accelerated elimination procedure [see Warnings and Precautions (5.3)].

5.10 Increased Blood Pressure

In placebo-controlled studies in adult patients, the mean change from baseline to the end of study in systolic blood pressure was +2.3 mmHg and +2.7 mmHg for AUBAGIO 7 mg and 14 mg, respectively, and -0.6 mmHg for placebo. The change from baseline in diastolic blood pressure was +1.4 mmHg and +1.9 mmHg for AUBAGIO 7 mg and 14 mg, respectively, and -0.3 mmHg for placebo. Hypertension was an adverse reaction in 3.1% and 4.3% of patients treated with 7 mg or 14 mg of AUBAGIO compared with 1.8% for placebo. Check blood pressure before start of AUBAGIO treatment and periodically thereafter. Elevated blood pressure should be appropriately managed during treatment with AUBAGIO.

5.11 Respiratory Effects

Interstitial lung disease, including acute interstitial pneumonitis, has been reported with AUBAGIO in the postmarketing setting.

Interstitial lung disease and worsening of pre-existing interstitial lung disease have been reported during treatment with leflunomide. Interstitial lung disease may be fatal and may occur acutely at any time during therapy with a variable clinical presentation. New onset or worsening pulmonary symptoms, such as cough and dyspnea, with or without associated fever, may be a reason for discontinuation of therapy and for further investigation as appropriate. If discontinuation of the drug is necessary, consider initiation of an accelerated elimination procedure [see Warnings and Precautions (5.3)].

5.12 Pancreatitis in Pediatric Patients

AUBAGIO is not approved for use in pediatric patients. In the pediatric clinical trial, cases of pancreatitis were observed in 1.8% (2/109) of patients receiving AUBAGIO; one of these cases was serious [see Use in Specific Populations (8.4)]. If pancreatitis is suspected, discontinue teriflunomide and start an accelerated elimination procedure [see Warnings and Precautions (5.3)].

5.13 Concomitant Use with Immunosuppressive or Immunomodulating Therapies

Coadministration with antineoplastic or immunosuppressive therapies used for treatment of multiple sclerosis has not been evaluated. Safety studies in which AUBAGIO was concomitantly administered with other immune modulating therapies for up to one year (interferon beta, glatiramer acetate) did not reveal any specific safety concerns. The long-term safety of these combinations in the treatment of multiple sclerosis has not been established.

In any situation in which the decision is made to switch from AUBAGIO to another agent with a known potential for hematologic suppression, it would be prudent to monitor for hematologic toxicity, because there will be overlap of systemic exposure to both compounds. Use of an accelerated elimination procedure may decrease this risk, but may also potentially result in return of disease activity if the patient had been responding to AUBAGIO treatment [see Warnings and Precautions (5.3)].

6 ADVERSE REACTIONS

The following clinically significant adverse reactions are described elsewhere in the prescribing information:

- Hepatotoxicity [see Contraindications (4) and Warnings and Precautions (5.1)]
- Bone Marrow Effects/Immunosuppression Potential/Infections [see Warnings and Precautions (5.4)]
- Hypersensitivity Reactions [see Contraindications (4) and Warnings and Precautions (5.5)]
- Serious Skin Reactions [see Warnings and Precautions (5.6)]
- Drug Reaction with Eosinophilia and Systemic Symptoms [see Warnings and Precautions (5.7)]
- Cutaneous or Mucocutaneous Ulcers and Impaired Wound Healing [see Warnings and Precautions (5.8)]
- Peripheral Neuropathy [see Warnings and Precautions (5.9)]
- Increased Blood Pressure [see Warnings and Precautions (5.10)]
- Respiratory Effects [see Warnings and Precautions (5.11)]
- Pancreatitis in Pediatric Patients [see Warnings and Precautions (5.12)]

6.1 Clinical Trials Experience

Because clinical trials are conducted under widely varying conditions, adverse reaction rates observed in the clinical trials of a drug cannot be directly compared to rates in the clinical trials of another drug and may not reflect the rates observed in clinical practice.

A total of 2047 patients receiving AUBAGIO (7 mg or 14 mg once daily) constituted the safety population in the pooled analysis of placebo-controlled studies in patients with relapsing forms of multiple sclerosis; of these, 71% were female. The average age was 37 years.

Table 1 lists adverse reactions in placebo-controlled trials with rates that were at least 2% for AUBAGIO patients and also at least 2% above the rate in placebo patients. The most common were headache, an increase in ALT, diarrhea, alopecia, and nausea. The adverse reaction most commonly associated with discontinuation was an increase in ALT (3.3%, 2.6%, and 2.3% of all patients in the AUBAGIO 7 mg, AUBAGIO 14 mg, and placebo treatment arms, respectively).

Table 1: Adverse Reactions in Pooled Placebo-Controlled Studies in Patients with Relapsing Forms of Multiple Sclerosis
Adverse Reaction | AUBAGIO 7 mg (N=1045) | AUBAGIO 14 mg (N=1002) | Placebo (N=997)
Headache | 18% | 16% | 15%
Increase in Alanine aminotransferase | 13% | 15% | 9%
Diarrhea | 13% | 14% | 8%
Alopecia | 10% | 13% | 5%
Nausea | 8% | 11% | 7%
Paresthesia | 8% | 9% | 7%
Arthralgia | 8% | 6% | 5%
Neutropenia | 4% | 6% | 2%
Hypertension | 3% | 4% | 2%

Cardiovascular Deaths

Four cardiovascular deaths, including three sudden deaths, and one myocardial infarction in a patient with a history of hyperlipidemia and hypertension were reported among approximately 2600 patients exposed to AUBAGIO in the premarketing database. These cardiovascular deaths occurred during uncontrolled extension studies, one to nine years after initiation of treatment. A relationship between AUBAGIO and cardiovascular death has not been established.

Acute Renal Failure

In placebo-controlled studies, creatinine values increased more than 100% over baseline in 8/1045 (0.8%) patients in the 7 mg AUBAGIO group and 6/1002 (0.6%) patients in the 14 mg AUBAGIO group versus 4/997 (0.4%) patients in the placebo group. These elevations were transient. Some elevations were accompanied by hyperkalemia. AUBAGIO may cause acute uric acid nephropathy with transient acute renal failure because AUBAGIO increases renal uric acid clearance.

Hypophosphatemia

In clinical trials, 18% of AUBAGIO-treated patients had hypophosphatemia with serum phosphorus levels of at least 0.6 mmol/L, compared to 7% of placebo-treated patients; 4% of AUBAGIO-treated patients had hypophosphatemia with serum phosphorus levels at least 0.3 mmol/L but less than 0.6 mmol/L, compared to 0.8% of placebo-treated patients. No patient in any treatment group had a serum phosphorus below 0.3 mmol/L.

6.2 Postmarketing Experience

The following adverse reactions have been identified during postapproval use of AUBAGIO. Because these reactions are reported voluntarily from a population of uncertain size, it is not always possible to reliably estimate their frequency or establish a causal relationship to drug exposure.

- Blood and Lymphatic System Disorders: Thrombocytopenia [see Warnings and Precautions (5.4)]
- Gastrointestinal Disorders: Pancreatitis, colitis
- Hepatobiliary Disorders: Drug-induced liver injury (DILI) [see Warnings and Precautions (5.1)]
- Immune System Disorders: Hypersensitivity reactions, some of which were severe, such as anaphylaxis and angioedema [see Warnings and Precautions (5.5)]
- Respiratory, Thoracic, and Mediastinal Disorders: Interstitial lung disease [see Warnings and Precautions (5.11)]
- Skin and Subcutaneous Tissue Disorders: Severe skin reactions, including toxic epidermal necrolysis and Stevens-Johnson syndrome [see Warnings and Precautions (5.6)]; drug reaction with eosinophilia and systemic symptoms (DRESS) [see Warnings and Precautions (5.7)]; psoriasis or worsening of psoriasis (including pustular psoriasis and nail psoriasis); nail disorders; cutaneous or mucocutaneous ulcers; impaired wound healing [see Warnings and Precautions (5.8)]

7 DRUG INTERACTIONS

Effect of AUBAGIO on CYP2C8 Substrates

Teriflunomide is an inhibitor of CYP2C8 in vivo. In patients taking AUBAGIO, exposure of drugs metabolized by CYP2C8 (e.g., paclitaxel, pioglitazone, repaglinide, rosiglitazone) may be increased. Monitor these patients and adjust the dose of the concomitant drug(s) metabolized by CYP2C8 as required [see Clinical Pharmacology (12.3)].

Effect of AUBAGIO on Warfarin

Coadministration of AUBAGIO with warfarin requires close monitoring of the international normalized ratio (INR) because AUBAGIO may decrease peak INR by approximately 25%.

Effect of AUBAGIO on Oral Contraceptives

AUBAGIO may increase the systemic exposures of ethinylestradiol and levonorgestrel. Consideration should be given to the type or dose of contraceptives used in combination with AUBAGIO [see Clinical Pharmacology (12.3)].

Effect of AUBAGIO on CYP1A2 Substrates

Teriflunomide may be a weak inducer of CYP1A2 in vivo. In patients taking AUBAGIO, exposure of drugs metabolized by CYP1A2 (e.g., alosetron, duloxetine, theophylline, tizanidine) may be reduced. Monitor these patients and adjust the dose of the concomitant drug(s) metabolized by CYP1A2 as required [see Clinical Pharmacology (12.3)].

Effect of AUBAGIO on Organic Anion Transporter 3 (OAT3) Substrates

Teriflunomide inhibits the activity of OAT3 in vivo. In patients taking AUBAGIO, exposure of drugs which are OAT3 substrates (e.g., cefaclor, cimetidine, ciprofloxacin, penicillin G, ketoprofen, furosemide, methotrexate, zidovudine) may be increased. Monitor these patients and adjust the dose of the concomitant drug(s) which are OAT3 substrates as required [see Clinical Pharmacology (12.3)].

Effect of AUBAGIO on BCRP and Organic Anion Transporting Polypeptide B1 and B3 (OATP1B1/1B3) Substrates

Teriflunomide inhibits the activity of BCRP and OATP1B1/1B3 in vivo. For a patient taking AUBAGIO, the dose of rosuvastatin should not exceed 10 mg once daily. For other substrates of BCRP (e.g., mitoxantrone) and drugs in the OATP family (e.g., methotrexate, rifampin), especially HMG-Co reductase inhibitors (e.g., atorvastatin, nateglinide, pravastatin, repaglinide, and simvastatin), consider reducing the dose of these drugs and monitor patients closely for signs and symptoms of increased exposures to the drugs while patients are taking AUBAGIO [see Clinical Pharmacology (12.3)].

8 USE IN SPECIFIC POPULATIONS

8.1 Pregnancy

Risk Summary

AUBAGIO is contraindicated for use in pregnant women and females of reproductive potential not using effective contraception because of the potential for fetal harm based on animal data [see Contraindications (4) and Warnings and Precautions (5.2)].

In animal reproduction studies in rat and rabbit, oral administration of teriflunomide during organogenesis caused teratogenicity and embryolethality at plasma exposures (AUC) lower than that at the maximum recommended human dose (MRHD) of 14 mg/day [see Data]. Available human data from pregnancy registries, clinical trials, pharmacovigilance cases, and published literature are too limited to draw any conclusions, but they do not clearly indicate increased birth defects or miscarriage associated with inadvertent teriflunomide exposure in the early first trimester when followed by an accelerated elimination procedure [see Clinical Considerations and Data]. There are no human data pertaining to exposures later in the first trimester or beyond.

In the US general population, the estimated background risk of major birth defects and miscarriage in clinically recognized pregnancies is 2%–4% and 15%–20%, respectively. The background risk of major birth defects and miscarriage in the indicated population is unknown.

There is a pregnancy surveillance program for AUBAGIO. If AUBAGIO exposure occurs during pregnancy, or if a patient becomes pregnant within 2 years following the last dose of AUBAGIO, healthcare providers and patients are encouraged to report pregnancies by calling 1-800-745-4447, option 2.

Clinical Considerations

Fetal/Neonatal adverse reactions

Lowering the plasma concentration of teriflunomide by instituting an accelerated drug elimination procedure as soon as pregnancy is detected may decrease the risk to the fetus from AUBAGIO. The accelerated drug elimination procedure includes verification that the plasma teriflunomide concentration is less than 0.02 mg/L [see Warnings and Precautions (5.3) and Clinical Pharmacology (12.3)].

Data

Human data

Available human data are limited. Prospectively reported data (from clinical trials and postmarketing reports) from >150 pregnancies in patients treated with teriflunomide and >300 pregnancies in patients treated with leflunomide have not demonstrated an increased rate of congenital malformations or miscarriage following teriflunomide exposure in the early first trimester when followed by an accelerated elimination procedure. Specific patterns of major congenital malformations in humans have not been observed. Limitations of these data include an inadequate number of reported pregnancies from which to draw conclusions, the short duration of drug exposure in reported pregnancies, which precludes a full evaluation of the fetal risks, incomplete reporting, and the inability to control for confounders (such as underlying maternal disease and use of concomitant medications).

Animal data

When teriflunomide (oral doses of 1, 3, or 10 mg/kg/day) was administered to pregnant rats throughout the period of organogenesis, high incidences of fetal malformation (primarily craniofacial, and axial and appendicular skeletal defects) and fetal death were observed at doses not associated with maternal toxicity. Adverse effects on fetal development were observed following dosing at various stages throughout organogenesis. Maternal plasma exposure at the no-effect level (1.0 mg/kg/day) for fetal developmental toxicity in rats was less than that in humans at the maximum recommended human dose (MRHD, 14 mg/day).

Administration of teriflunomide (oral doses of 1, 3.5, or 12 mg/kg/day) to pregnant rabbits throughout organogenesis resulted in high incidences of fetal malformation (primarily craniofacial, and axial and appendicular skeletal defects) and fetal death at doses associated with minimal maternal toxicity. Maternal plasma exposure at the no-effect dose (1.0 mg/kg/day) for fetal developmental toxicity in rabbits was less than that in humans at the MRHD.

In studies in which teriflunomide (oral doses of 0.05, 0.1, 0.3, 0.6, or 1.0 mg/kg/day) was administered to rats during gestation and lactation, decreased growth, eye and skin abnormalities, and high incidences of malformation (limb defects) and postnatal death were observed in the offspring at doses not associated with maternal toxicity. Maternal plasma exposure at the no-effect dose for prenatal and postnatal developmental toxicity in rats (0.10 mg/kg/day) was less than that in humans at the MRHD.

In animal reproduction studies of leflunomide, embryolethality and teratogenic effects were observed in pregnant rat and rabbit at or below clinically relevant plasma teriflunomide exposures (AUC). In published reproduction studies in pregnant mice, leflunomide was embryolethal and increased the incidence of malformations (craniofacial, axial skeletal, heart and great vessel). Supplementation with exogenous uridine reduced the teratogenic effects in pregnant mice, suggesting that the mode of action (inhibition of mitochondrial enzyme dihydroorotate dehydrogenase) is the same for therapeutic efficacy and developmental toxicity. At recommended doses in humans, teriflunomide and leflunomide result in a similar range of plasma concentrations of teriflunomide.

8.2 Lactation

Risk Summary

There are no data on the presence of AUBAGIO in human milk, the effects on the breastfed infant, or the effects on milk production. Teriflunomide was detected in rat milk following a single oral dose.

Because of the potential for adverse reactions in a breastfed infant from AUBAGIO, women should not breastfeed during treatment with AUBAGIO.

8.3 Females and Males of Reproductive Potential

Pregnancy Testing

Exclude pregnancy prior to initiation of treatment with AUBAGIO in females of reproductive potential. Advise females to notify their healthcare provider immediately if pregnancy occurs or is suspected during treatment [see Warnings and Precautions (5.2, 5.3) and Use in Specific Populations (8.1)].

Contraception

Females

Females of reproductive potential should use effective contraception while taking AUBAGIO. If AUBAGIO is discontinued, use of contraception should be continued until it is verified that plasma concentrations of teriflunomide are less than 0.02 mg/L (0.02 mcg/mL, the level expected to have minimal fetal risk, based on animal data).

Females of reproductive potential who wish to become pregnant should discontinue AUBAGIO and undergo an accelerated elimination procedure. Effective contraception should be used until it is verified that plasma concentrations of teriflunomide are less than 0.02 mg/L (0.02 mcg/mL) [see Warnings and Precautions (5.2, 5.3) and Use in Specific Populations (8.1)].

Males

AUBAGIO is detected in human semen. Animal studies to specifically evaluate the risk of male mediated fetal toxicity have not been conducted. To minimize any possible risk, men not wishing to father a child and their female partners should use effective contraception. Men wishing to father a child should discontinue use of AUBAGIO and either undergo an accelerated elimination procedure or wait until verification that the plasma teriflunomide concentration is less than 0.02 mg/L (0.02 mcg/mL) [see Warnings and Precautions (5.3)].

8.4 Pediatric Use

Safety and effectiveness in pediatric patients have not been established. Effectiveness of AUBAGIO for the treatment of relapsing form of multiple sclerosis in pediatric patients (10 to 17 years of age) was not established in an adequate and well-controlled clinical study in 166 patients (109 patients received once-daily doses of AUBAGIO and 57 patients received placebo) for up to 96 weeks.

Pancreatitis has been reported in adults in the postmarketing setting, but appears to occur at higher frequency in the pediatric population. In this pediatric study, cases of pancreatitis were reported in 1.8% (2/109) of patients who received AUBAGIO compared to no patients in the placebo group. All patients in the pediatric trial recovered or were recovering after treatment discontinuation and accelerated elimination procedure [see Warnings and Precautions (5.12)].

Additionally, elevated or abnormal blood creatine phosphokinase was reported in 6.4% of pediatric patients who received AUBAGIO compared to no patients in the placebo group.

Juvenile Animal Toxicity Data

Oral administration of teriflunomide (0, 0.3, 3, or 6 mg/kg/day) to young rats on postnatal days 21 to 70 resulted in suppression of immune function (T-cell dependent antibody response) at the mid and high doses, and adverse effects on male reproductive organs (reduced sperm count) and altered neurobehavioral function (increased locomotor activity) at the high dose. At the no-effect dose (0.3 mg/kg/day) for developmental toxicity in juvenile rats, plasma exposures were less than those in pediatric patients at the doses of AUBAGIO tested in the clinical study.

8.5 Geriatric Use

Clinical studies of AUBAGIO did not include patients over 65 years old.

8.6 Hepatic Impairment

No dosage adjustment is necessary for patients with mild and moderate hepatic impairment. The pharmacokinetics of teriflunomide in severe hepatic impairment has not been evaluated. AUBAGIO is contraindicated in patients with severe hepatic impairment [see Contraindications (4), Warnings and Precautions (5.1), and Clinical Pharmacology (12.3)].

8.7 Renal Impairment

No dosage adjustment is necessary for patients with mild, moderate, and severe renal impairment [see Clinical Pharmacology (12.3)].

10 OVERDOSAGE

There is no experience regarding teriflunomide overdose or intoxication in humans. Teriflunomide 70 mg daily up to 14 days was well tolerated by healthy subjects.

In the event of clinically significant overdose or toxicity, cholestyramine or activated charcoal is recommended to accelerate elimination [see Warnings and Precautions (5.3)].

11 DESCRIPTION

AUBAGIO (teriflunomide) is an oral de novo pyrimidine synthesis inhibitor of the DHO-DH enzyme, with the chemical name (Z)-2-Cyano-3-hydroxy-but-2-enoic acid-(4-trifluoromethylphenyl)-amide. Its molecular weight is 270.21, and the empirical formula is C12H9F3N2O2 with the following chemical structure:

Teriflunomide is a white to almost white powder that is sparingly soluble in acetone, slightly soluble in polyethylene glycol and ethanol, very slightly soluble in isopropanol and practically insoluble in water.

Teriflunomide is formulated as film-coated tablets for oral administration. AUBAGIO tablets contain 7 mg or 14 mg of teriflunomide and the following inactive ingredients: lactose monohydrate, corn starch, hydroxypropyl cellulose, microcrystalline cellulose, sodium starch glycolate, and magnesium stearate. The film coating for the 14 mg tablet is made of hypromellose, titanium dioxide, talc, polyethylene glycol and indigo carmine aluminum lake. In addition to these, the 7 mg tablet film coating includes iron oxide yellow.

12 CLINICAL PHARMACOLOGY

12.1 Mechanism of Action

Teriflunomide, an immunomodulatory agent with anti-inflammatory properties, inhibits dihydroorotate dehydrogenase, a mitochondrial enzyme involved in de novo pyrimidine synthesis. The exact mechanism by which teriflunomide exerts its therapeutic effect in multiple sclerosis is unknown but may involve a reduction in the number of activated lymphocytes in CNS.

12.2 Pharmacodynamics

Potential to Prolong the QT Interval

In a placebo-controlled thorough QT study performed in healthy adult subjects, there was no evidence that teriflunomide caused QT interval prolongation of clinical significance (i.e., the upper bound of the 90% confidence interval for the largest placebo-adjusted, baseline-corrected QTc was below 10 ms).

12.3 Pharmacokinetics

Teriflunomide is the principal active metabolite of leflunomide and is responsible for leflunomide's activity in vivo. At recommended doses, teriflunomide and leflunomide result in a similar range of plasma concentrations of teriflunomide.

Based on a population analysis of teriflunomide in healthy adult volunteers and adult MS patients, median t1/2 was approximately 18 and 19 days after repeated doses of 7 mg and 14 mg respectively. It takes approximately 3 months respectively to reach steady-state concentrations. The estimated AUC accumulation ratio is approximately 30 after repeated doses of 7 or 14 mg.

Absorption

Median time to reach maximum plasma concentrations is between 1 to 4 hours post dose following oral administration of teriflunomide.

Food does not have a clinically relevant effect on teriflunomide pharmacokinetics.

Distribution

Teriflunomide is extensively bound to plasma protein (>99%) and is mainly distributed in plasma. The volume of distribution is 11 L after a single intravenous (IV) administration.

Metabolism

Teriflunomide is the major circulating moiety detected in plasma. The primary biotransformation pathway to minor metabolites of teriflunomide is hydrolysis, with oxidation being a minor pathway. Secondary pathways involve oxidation, N-acetylation and sulfate conjugation.

Elimination

Teriflunomide is eliminated mainly through direct biliary excretion of unchanged drug as well as renal excretion of metabolites. Over 21 days, 60.1% of the administered dose is excreted via feces (37.5%) and urine (22.6%). After an accelerated elimination procedure with cholestyramine, an additional 23.1% was recovered (mostly in feces). After a single IV administration, the total body clearance of teriflunomide is 30.5 mL/h.

Drug Interaction Studies

Teriflunomide is not metabolized by Cytochrome P450 or flavin monoamine oxidase enzymes.

The potential effect of AUBAGIO on other drugs

CYP2C8 substrates

There was an increase in mean repaglinide Cmax and AUC (1.7- and 2.4-fold, respectively) following repeated doses of teriflunomide and a single dose of 0.25 mg repaglinide, suggesting that teriflunomide is an inhibitor of CYP2C8 in vivo. The magnitude of interaction could be higher at the recommended repaglinide dose [see Drug Interactions (7)].

CYP1A2 substrates

Repeated doses of teriflunomide decreased mean Cmax and AUC of caffeine by 18% and 55%, respectively, suggesting that teriflunomide may be a weak inducer of CYP1A2 in vivo [see Drug Interactions (7)].

OAT3 substrates

There was an increase in mean cefaclor Cmax and AUC (1.43- and 1.54-fold, respectively), following repeated doses of teriflunomide, suggesting that teriflunomide is an inhibitor of organic anion transporter 3 (OAT3) in vivo [see Drug Interactions (7)].

BCRP and OATP1B1/1B3 substrates

There was an increase in mean rosuvastatin Cmax and AUC (2.65- and 2.51-fold, respectively) following repeated doses of teriflunomide, suggesting that teriflunomide is an inhibitor of BCRP transporter and organic anion transporting polypeptide 1B1 and 1B3 (OATP1B1/1B3) [see Drug Interactions (7)].

Oral contraceptives

There was an increase in mean ethinylestradiol Cmax and AUC0-24 (1.58- and 1.54-fold, respectively) and levonorgestrel Cmax and AUC0-24 (1.33- and 1.41-fold, respectively) following repeated doses of teriflunomide [see Drug Interactions (7)].

Teriflunomide did not affect the pharmacokinetics of bupropion (a CYP2B6 substrate), midazolam (a CYP3A4 substrate), S-warfarin (a CYP2C9 substrate), omeprazole (a CYP2C19 substrate), and metoprolol (a CYP2D6 substrate).

The potential effect of other drugs on AUBAGIO

Potent CYP and transporter inducers: Rifampin did not affect the pharmacokinetics of teriflunomide.

Specific Populations

Hepatic impairment

Mild and moderate hepatic impairment had no impact on the pharmacokinetics of teriflunomide. The pharmacokinetics of teriflunomide in severe hepatic impairment has not been evaluated [see Contraindications (4), Warnings and Precautions (5.1), and Use in Specific Populations (8.6)].

Renal impairment

Severe renal impairment had no impact on the pharmacokinetics of teriflunomide [see Use in Specific Populations (8.7)].

Gender

In a population analysis, the clearance rate for teriflunomide is 23% less in females than in males.

Race

Effect of race on the pharmacokinetics of teriflunomide cannot be adequately assessed due to a low number of patients who self-identified as Black or African American, Asian, or other races in the clinical trials.

13 NONCLINICAL TOXICOLOGY

13.1 Carcinogenesis, Mutagenesis, Impairment of Fertility

Carcinogenesis

No evidence of carcinogenicity was observed in lifetime carcinogenicity bioassays in mouse and rat. In mouse, teriflunomide was administered orally at doses up to 12 mg/kg/day for up to 95–104 weeks; plasma teriflunomide exposures (AUC) at the highest dose tested are approximately 3 times that in humans at the maximum recommended human dose (MRHD, 14 mg/day). In rat, teriflunomide was administered orally at doses up to 4 mg/kg/day for up to 97–104 weeks; plasma teriflunomide AUCs at the highest doses tested are less than that in humans at the MRHD.

Mutagenesis

Teriflunomide was negative in the in vitro bacterial reverse mutation (Ames) assay, the in vitro HPRT assay, and in in vivo micronucleus and chromosomal aberration assays. Teriflunomide was positive in an in vitro chromosomal aberration assay in human lymphocytes, with and without metabolic activation. Addition of uridine (to supplement the pyrimidine pool) reduced the magnitude of the clastogenic effect; however, teriflunomide was positive in the in vitro chromosomal aberration assay, even in the presence of uridine.

4-Trifluoromethylaniline (4-TFMA), a minor metabolite of teriflunomide, was positive in the in vitro bacterial reverse mutation (Ames) assay, the in vitro HPRT assay, and the in vitro chromosomal aberration assay in mammalian cells. 4-TFMA was negative in in vivo micronucleus and chromosomal aberration assays.

Impairment of Fertility

Oral administration of teriflunomide (0, 1, 3, 10 mg/kg/day) to male rats prior to and during mating (to untreated females) resulted in no adverse effects on fertility; however, reduced epididymal sperm count was observed at the mid and high doses tested. The no-effect dose for reproductive toxicity in male rats (1 mg/kg) is less than the MRHD on a mg/m^2 basis.

Oral administration of teriflunomide (0, 0.84, 2.6, 8.6 mg/kg/day) to female rats, prior to and during mating (to untreated males) and continuing to gestation day 6, resulted in embryolethality, reduced fetal body weight, and/or malformations at all doses tested. Due to marked embryolethality at the highest dose tested, no fetuses were available for evaluation. The lowest dose tested is less than the MRHD on a mg/m^2 basis.

14 CLINICAL STUDIES

Four randomized, controlled, double-blind clinical trials established the efficacy of AUBAGIO in patients with relapsing forms of multiple sclerosis.

Study 1 was a double-blind, placebo-controlled clinical trial that evaluated once daily doses of AUBAGIO 7 mg and AUBAGIO 14 mg for up to 26 months in patients with relapsing forms of multiple sclerosis. Patients were required to have a diagnosis of multiple sclerosis exhibiting a relapsing clinical course, with or without progression, and to have experienced at least one relapse over the year preceding the trial or at least two relapses over the two years preceding the trial. Patients were required not to have received interferon-beta for at least four months, or any other multiple sclerosis medication for at least six months before entering the study, nor were these medications permitted during the study. Neurological evaluations were to be performed at screening, every 12 weeks until week 108, and after suspected relapses. MRI was to be performed at screening, and at week 24, 48, 72, and 108. The primary endpoint was the annualized relapse rate (ARR).

In Study 1, 1088 patients were randomized to receive AUBAGIO 7 mg (n=366), AUBAGIO 14 mg (n=359), or placebo (n=363). At entry, patients had an Expanded Disability Status Scale (EDSS) score ≤5.5. Patients had a mean age of 38 years, mean disease duration of 5 years, and mean EDSS at baseline of 2.7. A total of 91% of patients had relapsing remitting multiple sclerosis, and 9% had a progressive form of multiple sclerosis with relapses. The mean duration of treatment was 635, 627, and 631 days for AUBAGIO 7 mg, AUBAGIO 14 mg, and placebo, respectively. The percentage of patients who completed the study treatment period was 75%, 73%, and 71% for AUBAGIO 7 mg, AUBAGIO 14 mg, and placebo, respectively.

There was a statistically significant reduction in ARR for patients who received AUBAGIO 7 mg or AUBAGIO 14 mg, compared to patients who received placebo (see Table 2). There was a consistent reduction of the ARR noted in subgroups defined by sex, age group, prior multiple sclerosis therapy, and baseline disease activity.

There was a statistically significant reduction in the relative risk of disability progression at week 108 sustained for 12 weeks (as measured by at least a 1-point increase from baseline EDSS ≤5.5 or a 0.5 point increase for those with a baseline EDSS >5.5) in the AUBAGIO 14 mg group compared to placebo (see Table 2 and Figure 1).

The effect of AUBAGIO on several magnetic resonance imaging (MRI) variables, including the total lesion volume of T2 and hypointense T1 lesions, was assessed in Study 1. The change in total lesion volume from baseline was significantly lower in the AUBAGIO 7 mg and AUBAGIO 14 mg groups than in the placebo group. Patients in both AUBAGIO groups had significantly fewer gadolinium-enhancing lesions per T1-weighted scan than those in the placebo group (see Table 2).

Table 2: Clinical and MRI Results of Study 1
 | AUBAGIO 7 mg N=365 | AUBAGIO 14 mg N=358 | Placebo N=363
Clinical Endpoints
Annualized relapse rate | 0.370 (p=0.0002) | 0.369 (p=0.0005) | 0.539
Relative risk reduction | 31% | 31% | –
Percent of patients remaining relapse-free at week 108 | 53.7% | 56.5% | 45.6%
Percent disability progression at week 108 | 21.7% (p=0.084) | 20.2% (p=0.028) | 27.3%
Hazard ratio | 0.76 | 0.70 | –
MRI Endpoints
Median change from baseline in Total lesion volume [Total lesion volume: sum of T2 and hypointense T1 lesion volume in mL] (mL) at week 108 | 0.755 (p=0.0317) [p-values based on cubic root transformed data for total lesion volume] | 0.345 (p=0.0003) | 1.127
Mean number of Gd-enhancing T1-lesions per scan | 0.570 (p<0.0001) | 0.261 (p<0.0001) | 1.331

Figure 1: Kaplan-Meier Plot of Time to Disability Progression Sustained for 12 Weeks (Study 1)

Study 2 was a double-blind, placebo-controlled clinical trial that evaluated once daily doses of AUBAGIO 7 mg and AUBAGIO 14 mg for up to 40 months in patients with relapsing forms of multiple sclerosis. Patients were required to have a diagnosis of multiple sclerosis exhibiting a relapsing clinical course and to have experienced at least one relapse over the year preceding the trial, or at least two relapses over the two years preceding the trial. Patients were required not to have received any multiple sclerosis medication for at least three months before entering the trial, nor were these medications permitted during the trial. Neurological evaluations were to be performed at screening, every 12 weeks until completion, and after every suspected relapse. The primary end point was the ARR.

A total of 1165 patients received AUBAGIO 7 mg (n=407), AUBAGIO 14 mg (n=370), or placebo (n=388). Patients had a mean age of 38 years, a mean disease duration of 5 years, and a mean EDSS at baseline of 2.7. A total of 98% of patients had relapsing remitting multiple sclerosis, and 2% had a progressive form of multiple sclerosis with relapses. The mean duration of treatment was 552, 567, and 571 days for AUBAGIO 7 mg, AUBAGIO 14 mg, and placebo, respectively. The percentage of patients who completed the study treatment period was 67%, 66%, and 68% for AUBAGIO 7 mg, AUBAGIO 14 mg, and placebo, respectively.

There was a statistically significant reduction in the ARR for patients who received AUBAGIO 7 mg or AUBAGIO 14 mg compared to patients who received placebo (see Table 3). There was a consistent reduction of the ARR noted in subgroups defined by sex, age group, prior multiple sclerosis therapy, and baseline disease activity.

There was a statistically significant reduction in the relative risk of disability progression at week 108 sustained for 12 weeks (as measured by at least a 1-point increase from baseline EDSS ≤5.5 or a 0.5 point increase for those with a baseline EDSS >5.5) in the AUBAGIO 14 mg group compared to placebo (see Table 3 and Figure 2).

Table 3: Clinical Results of Study 2
 | AUBAGIO 7 mg N=407 | AUBAGIO 14 mg N=370 | Placebo N=388
Clinical Endpoints
Annualized relapse rate | 0.389 (p=0.0183) | 0.319 (p=0.0001) | 0.501
Relative risk reduction | 22% | 36% | –
Percent of patients remaining relapse-free at week 108 | 58.2% | 57.1% | 46.8%
Percent disability progression at week 108 | 21.1% (p=0.762) | 15.8% (p=0.044) | 19.7%
Hazard ratio | 0.96 | 0.69 | –

Figure 2: Kaplan-Meier Plot of Time to Disability Progression Sustained for 12 Weeks (Study 2)

Study 3 was a double-blind, placebo-controlled clinical trial that evaluated once daily doses of AUBAGIO 7 mg and AUBAGIO 14 mg for up to 108 weeks in patients with relapsing multiple sclerosis. Patients were required to have had a first clinical event consistent with acute demyelination occurring within 90 days of randomization with 2 or more T2 lesions at least 3 mm in diameter that were characteristic of multiple sclerosis. A total of 614 patients received AUBAGIO 7 mg (n=203), AUBAGIO 14 mg (n=214), or placebo (n=197). Patients had a mean age of 32 years, EDSS at baseline of 1.7, and mean disease duration of two months. The proportion of patients free of relapse was greater in the AUBAGIO 7 mg (70.5%, p<0.05) and AUBAGIO 14 mg (72.2%, p<0.05) groups than in the placebo group (61.7%).

The effect of AUBAGIO on MRI activity was also demonstrated in Study 4, a randomized, double-blind, placebo-controlled clinical trial of multiple sclerosis patients with relapse. In Study 4, MRI was to be performed at baseline, 6 weeks, 12 weeks, 18 weeks, 24 weeks, 30 weeks, and 36 weeks after treatment initiation. A total of 179 patients were randomized to AUBAGIO 7 mg (n=61), AUBAGIO 14 mg (n=57), or placebo (n=61). Baseline demographics were consistent across treatment groups. The primary endpoint was the average number of unique active lesions/MRI scan during treatment. The mean number of unique active lesions per brain MRI scan during the 36-week treatment period was lower in patients treated with AUBAGIO 7 mg (1.06) and AUBAGIO 14 mg (0.98) as compared to placebo (2.69), the difference being statistically significant for both (p=0.0234 and p=0.0052, respectively).

16 HOW SUPPLIED/STORAGE AND HANDLING

AUBAGIO is available as 7 mg and 14 mg tablets.

The 14 mg tablet is pale blue to pastel blue, pentagonal film-coated tablet with dose strength "14" imprinted on one side and engraved with corporate logo on the other side. Each tablet contains 14 mg of teriflunomide.

The 7 mg tablet is very light greenish-bluish grey to pale greenish-blue, hexagonal film-coated tablet with dose strength "7" imprinted on one side and engraved with corporate logo on the other side. Each tablet contains 7 mg of teriflunomide.

AUBAGIO 14 mg tablets are supplied as:

NDC 58468-0210-4 | Carton containing a bottle of 30 tablets
NDC 58468-0210-1 | Carton of 5 tablets with one blister card with five tablets

AUBAGIO 7 mg tablets are supplied as:

NDC 58468-0211-4 | Carton containing a bottle of 30 tablets
NDC 58468-0211-2 | Carton of 5 tablets with one blister card with five tablets

STORAGE AND HANDLING

Store at 68°F to 77°F (20°C to 25°C) with excursions permitted between 59°F and 86°F (15°C and 30°C).

17 PATIENT COUNSELING INFORMATION

Advise the patient to read the FDA-approved patient labeling (Medication Guide).

A Medication Guide is required for distribution with AUBAGIO.

Hepatotoxicity

Inform patients that AUBAGIO may cause liver injury, which can be life-threatening, and that their liver enzymes will be checked before starting AUBAGIO and at least monthly for 6 months after starting AUBAGIO [see Dosage and Administration (2) and Warnings and Precautions (5.1)]. Advise patients that they should contact their physician if they have any unexplained nausea, vomiting, abdominal pain, fatigue, anorexia, or jaundice and/or dark urine.

Embryofetal Toxicity

- Advise females of reproductive potential
  - of the potential for fetal harm if AUBAGIO is taken during pregnancy
  - to notify their healthcare provider immediately if a pregnancy occurs or is suspected
  - who are exposed to AUBAGIO during pregnancy or who become pregnant within 2 years following the last dose of AUBAGIO that there is a pregnancy safety surveillance program that monitors pregnancy outcomes. Encourage these patients to report their pregnancy by calling 1-800-745-4447, option 2 [see Use in Specific Populations (8.1)].
  - to use effective contraception during treatment with AUBAGIO and until the teriflunomide plasma concentration is verified to be less than 0.02 mg/L [see Warnings and Precautions (5.2, 5.3), Use in Specific Populations (8.1, 8.3), Clinical Pharmacology (12.3)].
- Instruct men taking AUBAGIO and not wishing to father a child to use effective contraception to minimize any possible risk to the fetus; their female partners should also use effective contraception.
- Advise men wishing to father a child to discontinue use of AUBAGIO and undergo an accelerated elimination procedure.

Availability of an Accelerated Elimination Procedure

Advise patients that AUBAGIO may stay in the blood for up to 2 years after the last dose and that an accelerated elimination procedure may be used if needed [see Warnings and Precautions (5.3)].

Risk of Infections

Inform patients that they may develop a lowering of their white blood cell counts and that their blood counts will be checked before starting AUBAGIO.

Inform patients that they may be more likely to get infections when taking AUBAGIO and that they should contact their physician if they develop symptoms of infection, particularly in case of fever [see Warnings and Precautions (5.4)].

Advise patients that the use of some vaccines should be avoided during treatment with AUBAGIO and for at least 6 months after discontinuation.

Hypersensitivity Reactions

Advise patients to discontinue AUBAGIO and seek immediate medical attention if any signs or symptoms of a hypersensitivity reaction occur [see Contraindications (4) and Warnings and Precautions (5.5)]. Signs and symptoms can include dyspnea, urticaria, angioedema involving the lips, eyes, throat, or tongue, or skin rash.

Serious Skin Reactions

Advise patients to discontinue AUBAGIO and seek immediate medical attention if any signs of a serious skin reaction, such as SJS or TEN, occur [see Warnings and Precautions (5.6)]. Signs and symptoms can include rash, mouth sores, blisters, or peeling skin.

DRESS/Multi-organ Hypersensitivity

Instruct patients and caregivers that a fever or rash associated with signs of other organ system involvement (e.g., lymphadenopathy, hepatic dysfunction) may be drug-related and should be reported to their healthcare provider immediately. AUBAGIO should be discontinued immediately if a serious hypersensitivity reaction is suspected [see Warnings and Precautions (5.7)].

Cutaneous and Mucocutaneous Ulcers and Impaired Wound Healing

Advise patients to seek medical attention if they develop cutaneous or mucocutaneous ulcers or experience impaired wound healing after a surgery [see Warnings and Precautions (5.8)].

Peripheral Neuropathy

Inform patients that they may develop peripheral neuropathy. Advise patients that they should contact their physician if they develop symptoms of peripheral neuropathy, such as numbness or tingling of hands or feet [see Warnings and Precautions (5.9)].

Increased Blood Pressure

Inform patients that AUBAGIO may increase blood pressure [see Warnings and Precautions (5.10)].

Lactation

Advise females not to breastfeed during treatment with AUBAGIO [see Use in Specific Populations (8.2)].

Manufactured for:
Genzyme Corporation
Cambridge, MA 02141
A SANOFI COMPANY

Medication Guide
AUBAGIO® (oh-BAH-gee-oh)
(teriflunomide)
tablets, for oral use

Read this Medication Guide before you start using AUBAGIO and each time you get a refill. There may be new information. This information does not take the place of talking with your healthcare provider about your medical condition or your treatment.

What is the most important information I should know about AUBAGIO?
AUBAGIO may cause serious side effects, including:

- Liver problems: AUBAGIO may cause serious liver problems, including liver failure that can be life-threatening and may require a liver transplant. Your risk of developing serious liver problems may be higher if you already have liver problems or take other medicines that also affect your liver. Your healthcare provider should do blood tests to check your liver:
  - within 6 months before you start taking AUBAGIO
  - 1 time a month for 6 months after you start taking AUBAGIO
  Call your healthcare provider right away if you have any of the following symptoms of liver problems:
  - nausea
  - vomiting
  - stomach pain
  - loss of appetite
  - tiredness
  - your skin or the whites of your eyes turn yellow
  - dark urine
- Harm to your unborn baby: AUBAGIO may cause harm to your unborn baby. Do not take AUBAGIO if you are pregnant. Do not take AUBAGIO unless you are using effective birth control.
  - If you are a female, you should have a pregnancy test before you start taking AUBAGIO. Use effective birth control during your treatment with AUBAGIO.
  - After stopping AUBAGIO, continue using effective birth control until you have blood tests to make sure your blood levels of AUBAGIO are low enough.
  - If you become pregnant while taking AUBAGIO or within 2 years after you stop taking it, tell your healthcare provider right away.
  - There is a pregnancy safety surveillance program for females who are exposed to AUBAGIO during pregnancy or who become pregnant within 2 years after their last dose of AUBAGIO. The purpose of the program is to collect information about the health of pregnant females exposed to AUBAGIO and their babies. If you become pregnant, talk to your healthcare provider about how you can take part in the program or call 1-800-745-4447, option 2.
  - For men taking AUBAGIO:
    - If your female partner plans to become pregnant, you should stop taking AUBAGIO and ask your healthcare provider how to quickly lower the levels of AUBAGIO in your blood.
    - If your female partner does not plan to become pregnant, you and your female partner should use effective birth control during your treatment with AUBAGIO. AUBAGIO remains in your blood after you stop taking it, so continue using effective birth control until AUBAGIO blood levels have been checked and they are low enough.

AUBAGIO may stay in your blood for up to 2 years after you stop taking it. Your healthcare provider can prescribe a medicine to help lower your blood levels of AUBAGIO more quickly. Talk to your healthcare provider if you want more information about this.

What is AUBAGIO?

- AUBAGIO is a prescription medicine used to treat relapsing forms of multiple sclerosis (MS), to include clinically isolated syndrome, relapsing-remitting disease, and active secondary progressive disease, in adults.
- It is not known if AUBAGIO is safe and effective in children.

Who should not take AUBAGIO?
Do not take AUBAGIO if you:

- have severe liver problems.
- are pregnant or are of childbearing age and not using effective birth control.
- have had an allergic reaction to leflunomide, teriflunomide, or any other ingredients in AUBAGIO. Please see the end of this Medication Guide for a complete list of ingredients in AUBAGIO.
- take a medicine called leflunomide.

Before you take AUBAGIO, tell your healthcare provider about all of your medical conditions, including if you:

- have liver or kidney problems.
- have a fever or infection, or you are unable to fight infections.
- have numbness or tingling in your hands or feet that is different from your MS symptoms.
- have diabetes.
- have had serious skin problems when taking other medicines.
- have breathing problems.
- have high blood pressure.
- have had recent surgery or are planning to have surgery.
- you have an unhealed wound.
- are breastfeeding or plan to breastfeed. It is not known if AUBAGIO passes into your breast milk. You and your healthcare provider should decide if you will take AUBAGIO or breastfeed. You should not do both.

Tell your healthcare provider about all the medicines you take, including prescription and over-the-counter medicines, vitamins, and herbal supplements. Using AUBAGIO and other medicines may affect each other causing serious side effects. AUBAGIO may affect the way other medicines work, and other medicines may affect how AUBAGIO works.
Especially tell your healthcare provider if you take medicines that could raise your chance of getting infections, including medicines used to treat cancer or to control your immune system.
Ask your healthcare provider or pharmacist for a list of these medicines if you are not sure.
Know the medicines you take. Keep a list of them to show your healthcare provider or pharmacist when you get a new medicine.

How should I take AUBAGIO?

- Take AUBAGIO exactly as your healthcare provider tells you to take it.
- Take AUBAGIO 1 time each day.
- Take AUBAGIO with or without food.

What are the possible side effects of AUBAGIO?
AUBAGIO may cause serious side effects, including:

- see "What is the most important information I should know about AUBAGIO?"
- decreases in your white blood cell count. Your white blood cell counts should be checked before you start taking AUBAGIO. When you have a low white blood cell count you:
  - may have more frequent infections. You should have a skin test for TB (tuberculosis) before you start taking AUBAGIO. Tell your healthcare provider if you have any of these symptoms of an infection:
    - fever
    - tiredness
    - body aches
    - chills
    - nausea
    - vomiting
  - should not receive certain vaccinations during your treatment with AUBAGIO and for 6 months after your treatment with AUBAGIO ends.
- allergic reactions. Stop taking AUBAGIO and call your healthcare provider right away or get emergency medical help if you have difficulty breathing, itching, swelling on any part of your body including in your lips, eyes, throat, or tongue.
- serious skin reactions. AUBAGIO may cause serious skin reactions that may lead to death. Stop taking AUBAGIO and call your healthcare provider right away or get emergency medical help if you have any of the following symptoms: rash or redness and peeling, mouth sores or blisters.
- other types of allergic reactions or serious problems that may affect different parts of the body such as your liver, kidneys, heart, or blood cells. You may or may not have a rash with these types of reactions. Other symptoms you may have are:
  - severe muscle pain
  - swollen lymph glands
  - swelling of your face
  - unusual bruising or bleeding
  - weakness or tiredness
  - yellowing of your skin or the white part of your eyes
  If you have a fever or rash with any of the above symptoms, stop taking AUBAGIO and call your healthcare provider right away.
- ulcers of the skin or mucous membranes (such as the eyes, nose, lips, mouth, or genitals) and impaired wound healing. AUBAGIO may cause ulcers and impaired wound healing. Tell your healthcare provider right away if any of the following happen:
  - you develop ulcers during treatment with AUBAGIO
  - you experience impaired wound healing during treatment with AUBAGIO
  - you are going to have surgery
  - you still have an unhealed wound following surgery
- numbness or tingling in your hands or feet that is different from your MS symptoms. You have a higher chance of getting these symptoms if you:
  - are over 60 years of age
  - take certain medicines that affect your nervous system
  - have diabetes
  Tell your healthcare provider if you have numbness or tingling in your hands or feet that is different from your MS.
- high blood pressure. Your healthcare provider should check your blood pressure before you start taking AUBAGIO and while you are taking AUBAGIO.
- new or worsening breathing problems. These may be serious and lead to death. Call your healthcare provider right away or get emergency medical help if you have shortness of breath or coughing with or without fever.

The most common side effects of AUBAGIO include:

- headache
- diarrhea
- nausea
- hair thinning or loss (alopecia)
- increases in the results of blood tests to check your liver function

These are not all the possible side effects of AUBAGIO. For more information, ask your healthcare provider or pharmacist.
Call your healthcare provider for medical advice about side effects. You may report side effects to FDA at 1-800-FDA-1088.

How should I store AUBAGIO?

- Store AUBAGIO at room temperature between 68°F to 77°F (20°C to 25°C).
- Keep AUBAGIO and all medicines out of the reach of children.

General information about the safe and effective use of AUBAGIO.
Medicines are sometimes prescribed for purposes other than those listed in a Medication Guide. Do not use AUBAGIO for a condition for which it was not prescribed. Do not give AUBAGIO to other people, even if they have the same symptoms you have. It may harm them.
You can ask your healthcare provider or pharmacist for information about AUBAGIO that is written for health professionals.

What are the ingredients in AUBAGIO?
Active ingredient: teriflunomide
Inactive ingredients in 7 mg and 14 mg tablets: lactose monohydrate, corn starch, hydroxypropyl cellulose, microcrystalline cellulose, sodium starch glycolate, magnesium stearate, hypromellose, titanium dioxide, talc, polyethylene glycol and indigo carmine aluminum lake.
In addition, the 7 mg tablets also contain iron oxide yellow.
For more information, go to www.aubagio.com or call Genzyme Medical Information Services at 1-800-745-4447, option 2.

Manufactured for:
Genzyme Corporation
Cambridge, MA 02141
A SANOFI COMPANY

This Medication Guide has been approved by the U.S. Food and Drug Administration.

Revised: 2/2026

PRINCIPAL DISPLAY PANEL - 7 mg Tablet Bottle Carton

NDC 58468-0211-4

Aubagio®
(teriflunomide)
Tablets

7 mg

Rx only

Dispense with Medication Guide

30 Tablets

sanofi

PRINCIPAL DISPLAY PANEL - 14 mg Tablet Bottle Carton

NDC 58468-0210-4

Aubagio®
(teriflunomide)
Tablets

14 mg

Rx only

Dispense with Medication Guide

30 Tablets

sanofi